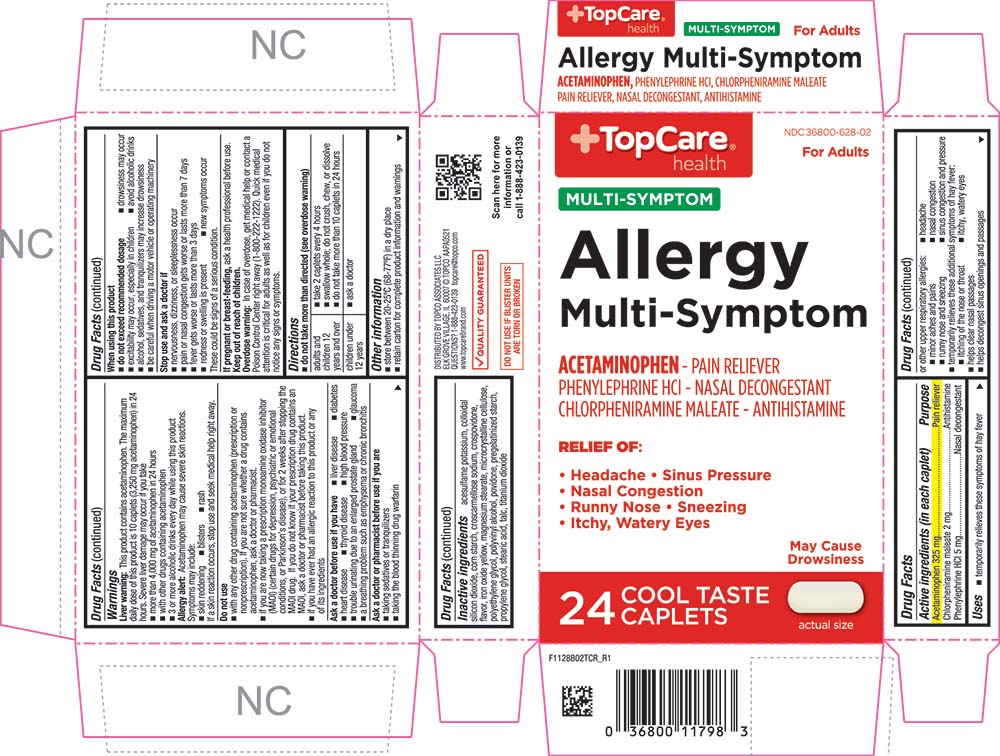 DRUG LABEL: Allergy Multi Symptom
NDC: 36800-628 | Form: TABLET, COATED
Manufacturer: TOPCO ASSOCIATES LLC
Category: otc | Type: HUMAN OTC DRUG LABEL
Date: 20241203

ACTIVE INGREDIENTS: ACETAMINOPHEN 325 mg/1 1; CHLORPHENIRAMINE MALEATE 2 mg/1 1; PHENYLEPHRINE HYDROCHLORIDE 5 mg/1 1
INACTIVE INGREDIENTS: ACESULFAME POTASSIUM; SILICON DIOXIDE; CROSCARMELLOSE SODIUM; FERRIC OXIDE YELLOW; MAGNESIUM STEARATE; CROSPOVIDONE; CELLULOSE, MICROCRYSTALLINE; POLYETHYLENE GLYCOL, UNSPECIFIED; POLYVINYL ALCOHOL, UNSPECIFIED; POVIDONE, UNSPECIFIED; STARCH, CORN; PROPYLENE GLYCOL; STEARIC ACID; TALC; TITANIUM DIOXIDE

1128B-TCR-2021-1112

Drug Facts

ACTIVE INGREDIENT

Active ingredients (in each caplet) | Purpose
Acetaminophen 325 mg | Pain reliever
Chlorpheniramine maleate 2 mg | Antihistamine
Phenylephrine HCl 5 mg | Nasal decongestant

Uses

- temporarily relieves these symptoms of hay fever or other upper respiratory allergies:
  - headache
  - sinus congestion and pressure
  - nasal congestion
  - runny nose and sneezing
  - minor aches and pains
- temporarily relieves these additional symptoms of hay fever:
  - itching of the nose or throat
  - itchy, watery eyes
- helps clear nasal passages
- helps decongest sinus openings and passages

Warnings

Liver warning

This product contains acetaminophen. The maximum daily dose of this product is 10 caplets (3,250 mg acetaminophen) in 24 hours. Severe liver damage may occur if you take

- more than 4,000 mg of acetaminophen in 24 hours
- with other drugs containing acetaminophen
- 3 or more alcoholic drinks every day while using this product

Allergy alert

Acetaminophen may cause severe skin reactions. Symptoms may include:

- skin reddening
- blisters
- rash

If a skin reaction occurs, stop use and seek medical help right away.

Do not use

- with any other drug containing acetaminophen (prescription or nonprescription). If you are not sure whether a drug contains acetaminophen, ask a doctor or pharmacist.
- if you are now taking a prescription monoamine oxidase inhibitor (MAOI) (certain drugs for depression, psychiatric or emotional conditions, or Parkinson's disease), or for 2 weeks after stopping the MAOI drug. If you do not know if your prescription drug contains an MAOI, ask a doctor or pharmacist before taking this product.
- if you have ever had an allergic reaction to this product or any of its ingredients

Ask a doctor before use if you have

- liver disease
- heart disease
- high blood pressure
- thyroid disease
- diabetes
- trouble urinating due to an enlarged prostate gland
- a breathing problem such as emphysema or chronic bronchitis
- glaucoma

Ask a doctor or pharmacist before use if you are

- taking sedatives or tranquilizers
- taking the blood thinning drug warfarin

When using this product

- do not exceed recommended dosage
- excitability may occur, especially in children
- drowsiness may occur
- alcohol, sedatives, and tranquilizers may increase drowsiness
- avoid alcoholic drinks
- be careful when driving a motor vehicle or operating machinery

Stop use and ask a doctor if

- nervousness, dizziness, or sleeplessness occur
- pain or nasal congestion gets worse or lasts more than 7 days
- fever gets worse or lasts more than 3 days
- redness or swelling is present
- new symptoms occur

These could be signs of a serious condition.

PREGNANCY OR BREAST FEEDING

If pregnant or breast-feeding, ask a health professional before use.

Keep out of reach of children.

Overdose warning

In case of overdose, get medical help or contact a Poison Control Center right away (1-800-222-1222). Quick medical attention is critical for adults as well as for children even if you do not notice any signs or symptoms.

Directions

- do not take more than directed (see overdose warning)

adults and children 12 years and over | - take 2 caplets every 4 hours - swallow whole; do not crush, chew, or dissolve - do not take more than 10 caplets in 24 hours
children under 12 years | - ask a doctor

Other information

- store between 20°-25°C (68°-77°F) in a dry place
- retain carton for complete product information and warnings

Inactive ingredients

acesulfame potassium, colloidal silicon dioxide, corn starch, croscarmellose sodium, crospovidone, flavor, iron oxide yellow, magnesium stearate, microcrystalline cellulose, polyethylene glycol, polyvinyl alcohol, povidone, pregelatinized starch, propylene glycol, stearic acid, talc, titanium dioxide

PRINCIPAL DISPLAY PANEL

TopCare® health

NDC 36800-628-02

For Adults

MULTI-SYMPTOM

Allergy Multi-Symptom

ACETAMINOPHEN - PAIN RELIEVER

PHENYLEPHRINE HCl - NASAL DECONGESTANT

CHLORPHENIRAMINE MALEATE - ANTIHISTAMINE

RELIEF OF:

• Headache

• Sinus Pressure

• Nasal Congestion

• Runny Nose

• Sneezing

• Itchy, Watery Eyes

May Cause Drowsiness

24 COOL TASTE CAPLETS

actual size